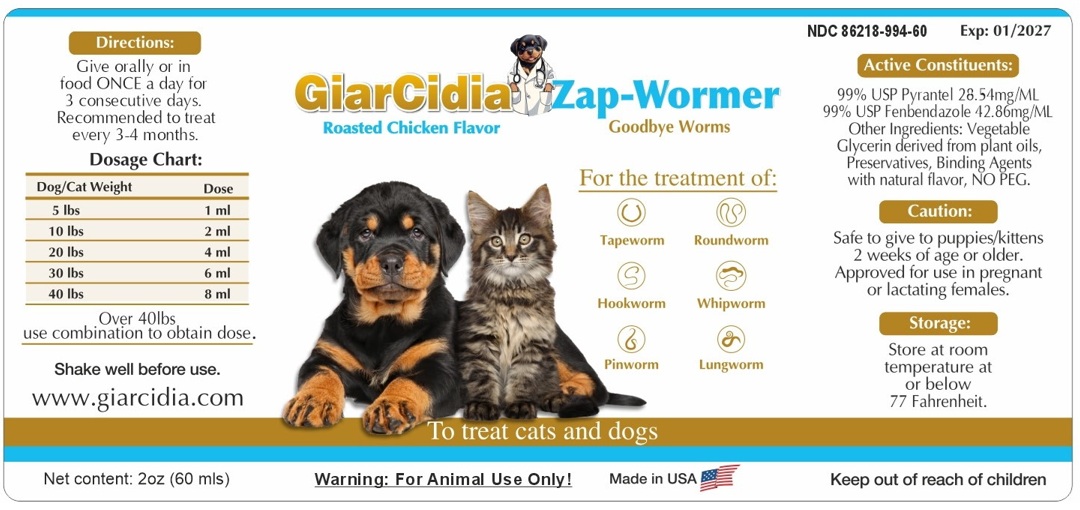 DRUG LABEL: GiarCidia Zap-Wormer
NDC: 86218-994 | Form: LIQUID
Manufacturer: GiarCidia LLC
Category: animal | Type: OTC ANIMAL DRUG LABEL
Date: 20250603

ACTIVE INGREDIENTS: PYRANTEL 28.54 mg/1 mL; FENBENDAZOLE 42.86 mg/1 mL
INACTIVE INGREDIENTS: GLYCERIN; POTASSIUM SORBATE; SODIUM BENZOATE; CELLULOSE SODIUM PHOSPHATE

GiarCidia Zap-Wormer

Active Constituents:

99% USP Pyrantel 28.54mg/ML
99% USP Fenbendazole 42.86mg/ML

Other Ingredients:

Vegetable Glycerin derived from plant oils, Preservatives, Binding Agents with natural flavor, NO PEG.

Caution:

Safe to give to puppies/kittens 2 weeks of age or older. Approved for use in pregnant or lactating females.

Keep out of reach of children

Storage:

Store at room temperature at or below 77 Fahrenheit.

Directions:

Give orally or in food ONCE a day for 3 consecutive days. Recommended to treat every 3-4 months.

Dosage Chart:
Dog/Cat Weight | Dose
5 lbs | 1 ml
10 lbs | 2 ml
20 lbs | 4 ml
30 lbs | 6 ml
40 lbs | 8 ml
Over 40lbs
use combination to obtain dose.

Shake well before use.

Roasted Chicken Flavor

Goodbye Worms

To treat cats and dogs

For the treatment of:

Tapeworm Roundworm
Hookworm Whipworm
Pinworm Lungworm

Warning: For Animal Use Only!

Made in USA

www.giarcidia.com